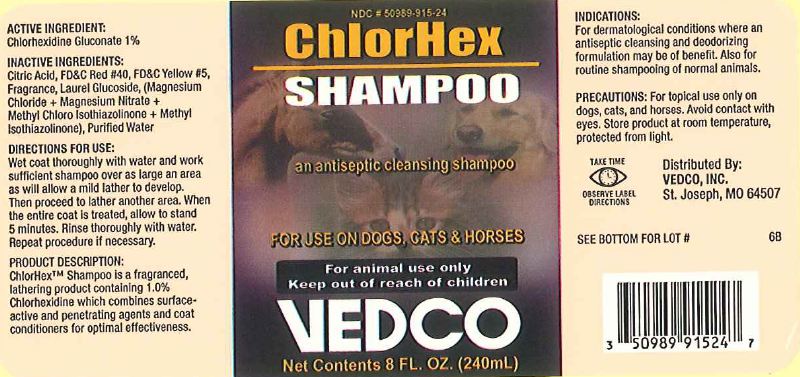 DRUG LABEL: ChlorHex
NDC: 50989-915 | Form: SHAMPOO
Manufacturer: Vedco, Inc
Category: animal | Type: OTC ANIMAL DRUG LABEL
Date: 20120203

ACTIVE INGREDIENTS: CHLORHEXIDINE GLUCONATE 10.0 g/1.0 L

ChlorHex Shampoo

Active ingredient(s)

Chlorhexidine Gluconate 1%

Purpose:

An antiseptic cleansing shampoo

Use:

For use on dogs, cats & horses

Warnings:

Avoid Contact with eyes

Precautions:

For topical use only on dogs, cats and horses

Keep out of reach of children

Directions for Use:

Wet coat thoroughly with water and work sufficient shampoo over as large an area as will allow a mild lather to develop. Then proceed to lather another area. When the entire coat is treated, allow to stand 5 minutes. Rinse thoroughly with water. Repeat procedure if necessary.

For Animal Use Only

Storage:

Store product at room temperature, protected from light.

Indications:

For dermatological conditions where an antiseptic cleansing and deodorizing formulation may be of benefit. Also for routine shampooing of normal animals.

Inactive Ingredients:

Citric Acid, FD&C Red #40, FD&C Yellow #5, Fragrance, Laurel Glucoside, (Magnesium Chloride + Magnesium Nitrate + Methyl Chloro Isothiazoline + Methyl Isothiazolinone), Purified Water

Principal Display Panel:

ChlorHex Shampoo